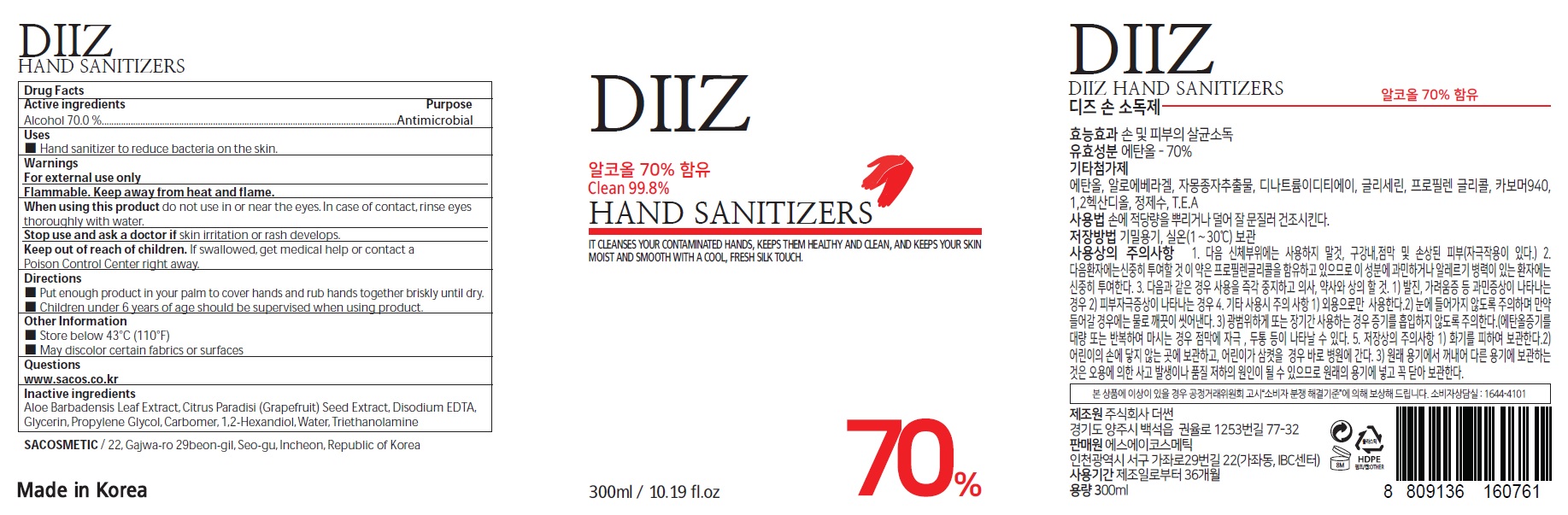 DRUG LABEL: DIIZ Hand Sanitizer
NDC: 74923-090 | Form: GEL
Manufacturer: THE SUN CO.LTD
Category: otc | Type: HUMAN OTC DRUG LABEL
Date: 20200604

ACTIVE INGREDIENTS: Alcohol 210 mL/300 mL
INACTIVE INGREDIENTS: ALOE VERA LEAF; Water; CITRUS PARADISI SEED; EDETATE DISODIUM ANHYDROUS; Glycerin; Propylene Glycol; CARBOMER HOMOPOLYMER, UNSPECIFIED TYPE; TROLAMINE

ACTIVE INGREDIENT

Alcohol 70.0%

INACTIVE INGREDIENT

Aloe Barbadensis Leaf Extract, Citrus Paradisi (Grapefruit) Seed Extract, Disodium EDTA, Glycerin, Propylene Glycol, Carbomer, 1,2-Hexandiol, Water, Triethanolamine

PURPOSE

Antimicrobial

WARNINGS

For external use only

Flammable. Keep away from heat and flame.

When using this product
Do not use in or near the eyes.
In case of contact, rinse eyes, thoroughly with water.

Stop use and ask a doctor if skin irritation or rash develops.

KEEP OUT OF REACH OF CHILDREN

If swallowed, get medical help or contact a Poison Control Center right away.

Uses

■ Hand sanitizer to reduce bacteria on the skin.

Directions

■ Put enough product in your palm to cover hands and rub hands together briskly until dry.

■ Children under 6 years of age should be supervised when using product.

Other Information

■ Store below 43°C (110°F)
■ May discolor certain fabrics or surfaces

QUESTIONS

www.sacos.co.kr